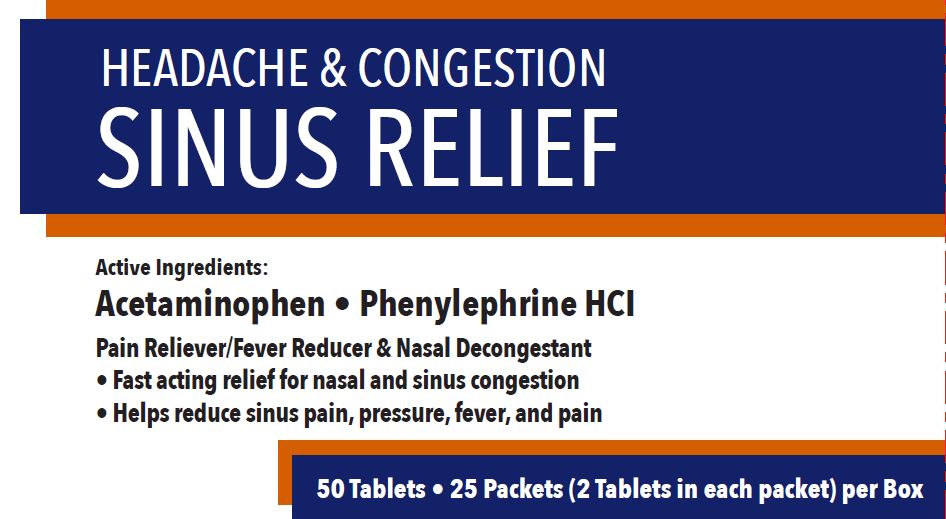 DRUG LABEL: First Aid Direct Headache and Congestion Sinus Relief
NDC: 42961-126 | Form: TABLET
Manufacturer: Cintas Corporation
Category: otc | Type: HUMAN OTC DRUG LABEL
Date: 20250925

ACTIVE INGREDIENTS: ACETAMINOPHEN 500 mg/1 1; PHENYLEPHRINE HYDROCHLORIDE 5 mg/1 1
INACTIVE INGREDIENTS: STARCH, CORN; CROSPOVIDONE; HYPROMELLOSE, UNSPECIFIED; MICROCRYSTALLINE CELLULOSE; POLYETHYLENE GLYCOL, UNSPECIFIED; POVIDONE; STEARIC ACID

First Aid Direct Headache and Congestion Sinus Relief

Active ingredients (in each tablet)

Acetaminophen 500 mg

Phenylephrine HCl 5 mg

Purpose

Pain reliever/fever reducer

Nasal decongestant

Uses

temporarily relieves these symptoms associated with hay fever or other respiratory allergies, and the common cold:

- sinus congestion and pressure
- headache
- minor aches and pains
- nasal congestion
- promotes sinus drainage
- temporarily reduces fever

Warnings

Liver warning: This product contains acetaminophen. Severe liver damage may occur if you take

- more than 4,000 mg of acetaminophen in 24 hours
- with other drugs containing acetaminophen
- adult has 3 or more alcoholic drinks every day while using this product

Allergy alert: acetaminophen may cause severe skin reactions. Symptoms may include:

- skin reddening
- blisters
- rash

If a skin reaction occurs, stop use and seek medical help right away.

Do not use

- with any other drug containing acetaminophen (prescription or nonprescription). If you are not sure whether a drug contains acetaminophen, ask a doctor or pharmacist.
- you are now taking a prescription monoamine oxidase inhibitor (MAOI) (certain drugs for depression, psychiatric or emotional conditions, or Parkinson's disease), or for 2 weeks after stopping the MAOI drug. If you do not know if your prescription drug contains an MAOI, ask a doctor or pharmacist before taking this product.
- if you are allergic to acetaminophen or any of the inactive ingredients in this product.

Ask a doctor before use if you have

- liver disease
- heart disease
- high blood pressure
- thyroid disease
- diabetes
- trouble urinating due to an enlarged prostate gland

Ask a doctor before use if you are taking the blood thining drug warfarin.

Stop use and ask doctor if

- nervousness, dizziness, or sleplessness occur
- pain or nasal congestion gets worse or lasts more than 7 days
- pain gets worse or lasts more than 10 days
- fever gets worse or lasts more than 3 days
- redness or swelling is present
- new symptoms occur

These could be signs of a serious condition.

PREGNANCY OR BREAST FEEDING

If pregnant or breast-feeding, ask a health professional before use.

Keep out of reach of children.

Overdose warning: In case of overdose, get medical help or contact a Poison Control Center (1-800-222-1222) right away. Quick medical attention is critical for adults as well as for children even if you do not notice any signs or symptoms.

Directions

- adults and children 12 years and older: • take 2 tablets every 6 hours • do not take more than 8 tablets in 24 hours
- children under 12 years of age: ask a doctor

Other information

- store at room temperature between 20-25°C (68-77°F)
- do not use if packet is open or torn

Inactive ingredients

corn starch, crospovidone, hypromellose, microcrystalline cellulose, polyethylene glycol, povidone, pregelatinized starch, stearic acid

Questions?

Call 1-800-327-2704 M-F 8AM-5PM

Principal Display Panel - 42961-126-02

HEADACHE & CONGESTION

SINUS RELIEF

Active Ingredients:

Acetaminophen • Phenylephrine HCl

Pain Reliever/Fever Reducer & Nasal Decongestant

- Fast acting relief for nasal and sinus congestion
- Helps reduce sinus pain, pressure, fever, and pain

50 Tablets • 25 Packets (2 Tablets in each packet) per Box